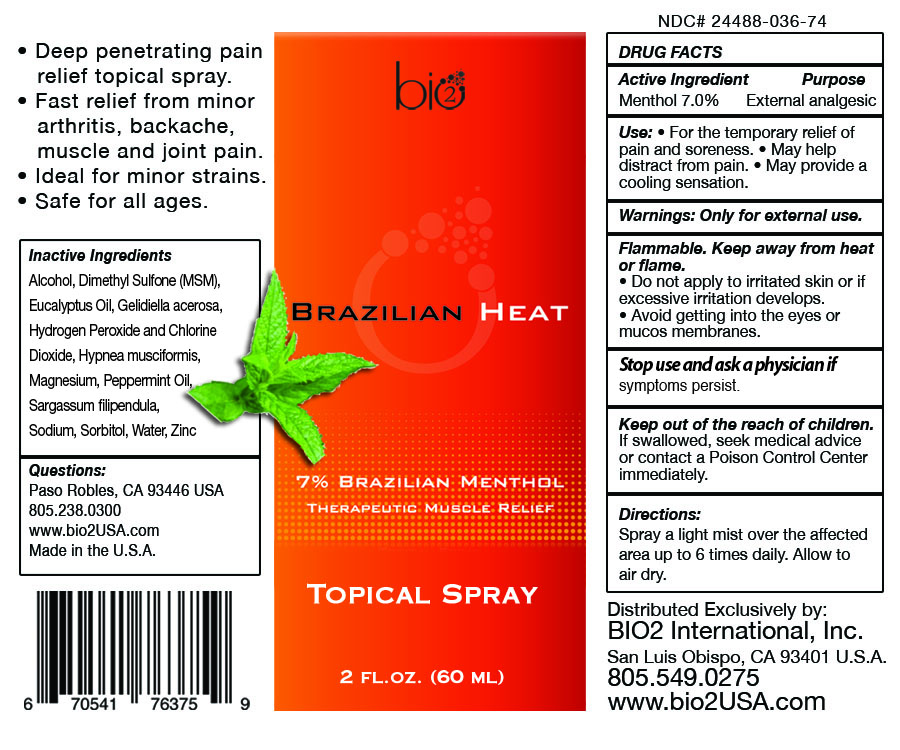 DRUG LABEL: Bio 2 Brazilian Heat
NDC: 24488-036 | Form: LIQUID
Manufacturer: Bio 2
Category: otc | Type: HUMAN OTC DRUG LABEL
Date: 20120315

ACTIVE INGREDIENTS: Menthol 4.2 mL/60 mL
INACTIVE INGREDIENTS: ALCOHOL; DIMETHYL SULFONE; EUCALYPTUS OIL; GELIDIELLA ACEROSA; HYDROGEN PEROXIDE; CHLORINE DIOXIDE; HYPNEA MUSCIFORMIS; MAGNESIUM; PEPPERMINT OIL; SARGASSUM FILIPENDULA; SODIUM; SORBITOL; WATER; ZINC

Drug Facts

Active Ingredient

Menthol 7.0%

Purpose

External analgesi

Use

- For the temporary relief of pain and soreness.
- May help distract from pain.
- May provide a cooling sensation.

Warnings

Only for external use.

Flammable. Keep away from heat
or flame.

- Do not apply to irritated skin or if
  excessive irritation develops
- Avoid getting into the eyes or
  mucos membranes.

Stop use and ask a physician if

Stop use and ask a physician
symptoms persist.

Keep out of reach of children

If swallowed, seek medical advice
or contact a Poison Control Center
immediately.

Directions

Spray a light mist over the affected
area up to 6 times daily. Allow to
air dry.

INACTIVE INGREDIENT

Alcohol, Dimethyl Sulfone (MSM),
Eucalyptus Oil, Gelidiella acerosa,
Hydrogen Peroxide and Chlorine
Dioxide, Hypnea musciformis,
Magnesium, Peppermint Oil,
Sargassum filipendula,
Sodium, Sorbitol, Water, Zinc

Questions:

Paso Robles, CA 93446 USA
805.238.0300
www.bio2USA.com
Made in the U.S.A.

PACKAGE LABEL

Placeholder Text